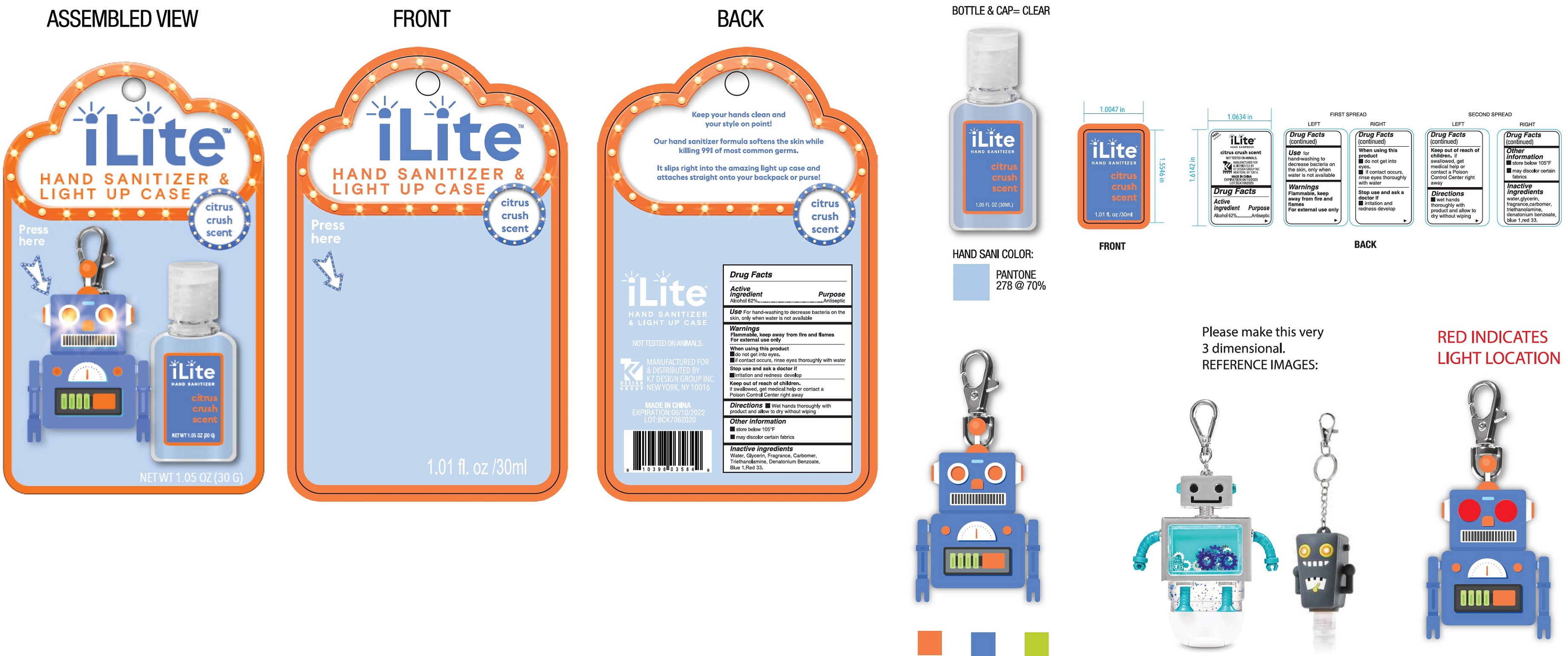 DRUG LABEL: citrus crush scent hand sanitizer robot
NDC: 74177-034 | Form: GEL
Manufacturer: K7 DESIGN GROUP INC
Category: otc | Type: HUMAN OTC DRUG LABEL
Date: 20231026

ACTIVE INGREDIENTS: ALCOHOL 0.62 mL/1 mL
INACTIVE INGREDIENTS: WATER; GLYCERIN; CARBOMER HOMOPOLYMER, UNSPECIFIED TYPE; TROLAMINE; DENATONIUM BENZOATE; FD&C BLUE NO. 1; D&C RED NO. 33

citrus crush scent hand sanitizer - robot

Active ingredient

Alcohol 62%

Purpose

Antiseptic

Use

For hand-washing to decrease bacteria on the skin, only when water is not available

Warnings

Flammable, keep away from fire and flames

For external use only

When using this product

- do not get into eyes.
- if contact occurs, rinse eyes thoroughly with water

Stop use and ask a doctor if

- irritation and redness develop

Keep out of reach of children.

if swallowed, get medical help or contact a Poison Control Center right away

Directions

- Wet hands thoroughly with product and allow to dry without wiping

Other information

- store below 105 °F
- may discolor certain fabrics

Inactive ingredients

Water, Glycerin, Fragrance, Carbomer, Triethanolamine, Denatonium Benzoate, Blue 1,Red 33.